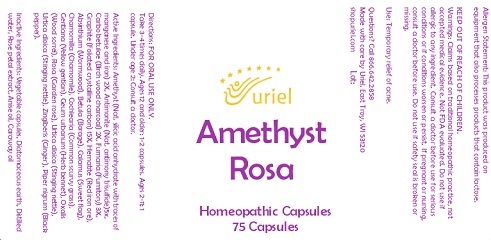 DRUG LABEL: Amethyst Rosa
NDC: 48951-1361 | Form: CAPSULE
Manufacturer: Uriel Pharmacy, Inc.
Category: homeopathic | Type: HUMAN OTC DRUG LABEL
Date: 20230420

ACTIVE INGREDIENTS: SILICON DIOXIDE 2 [hp_X]/1 g; GRAPHITE 15 [hp_X]/1 g; ANTIMONY TRISULFIDE 5 [hp_X]/1 g; ACTIVATED CHARCOAL 2 [hp_X]/1 g; FUMARIA OFFICINALIS FLOWERING TOP 3 [hp_X]/1 g
INACTIVE INGREDIENTS: WATER; WORMWOOD; URTICA DIOICA LEAF; BLACK PEPPER; DIATOMACEOUS EARTH; ACORUS CALAMUS ROOT; COCHLEARIA OFFICINALIS FLOWERING TOP; GENTIANA LUTEA ROOT; BETULA PUBESCENS BARK; GINGER; URTICA DIOICA ROOT; CARAWAY OIL; ROSA RUGOSA FLOWER; ANISE OIL; GEUM URBANUM ROOT; SEDUM ROSEUM WHOLE; POWDERED CELLULOSE; CHAMOMILE; OXALIS STRICTA WHOLE; FERRIC OXIDE RED

Amethyst Rosa

INDICATIONS AND USAGE

Directions: FOR ORAL USE ONLY.

DOSAGE AND ADMINISTRATION

Take 3-4 times daily. Ages 12 and older: 1-2 capsules. Ages 2-11: 1 capsule. Under age 2: Consult a doctor.

ACTIVE INGREDIENT

Active Ingredients: Amethyst (Nat. silicic acid anhydrate with traces of manganese and iron) 2X, Antimonite (Nat. antimony trisulfide)5x, Carbo betulae (Birch wood charcoal) 2X, Fumaria (Fumitory) 3X, Graphite (Foliated crystalline carbon) 15X.

INACTIVE INGREDIENT

Inactive Ingredients: Vegetable capsules, Diatomaceous earth, Distilled water, Rose petal extract, Anise oil, Caraway oil
Hematite (Red iron ore), Absinthium (Wormwood), Betula (Borage), Calamus (Sweet flag), Chamomilla (Chamomile), Cochlearia (Common scurvy grass), Gentiana (Yellow gentian), Geum urbanum (Herb bennet), Oxalis (Wood sorrel), Rosa (Garden rose), Urtica dioica (Stinging nettle), Urtica dioica (Stinging nettle), Zingiberis (Ginger), Piper nigrum (Black pepper).

PURPOSE

Use: Temporary relief of acne.

KEEP OUT OF REACH OF CHILDREN.

WARNINGS

Allergen Statement: This product was produced on equipment that also processes products that contain lactose.

Warnings: Claims based on traditional homeopathic practice, not accepted medical evidence. Not FDA evaluated. Do not use if allergic to any ingredient. Consult a doctor before use for serious conditions or if conditions worsen or persist. If pregnant or nursing, consult a doctor before use. Do not use if safety seal is broken or missing.

Questions? Call 866.642.2858
Made with care by Uriel, East Troy, WI 53120
shopuriel.com Lot: